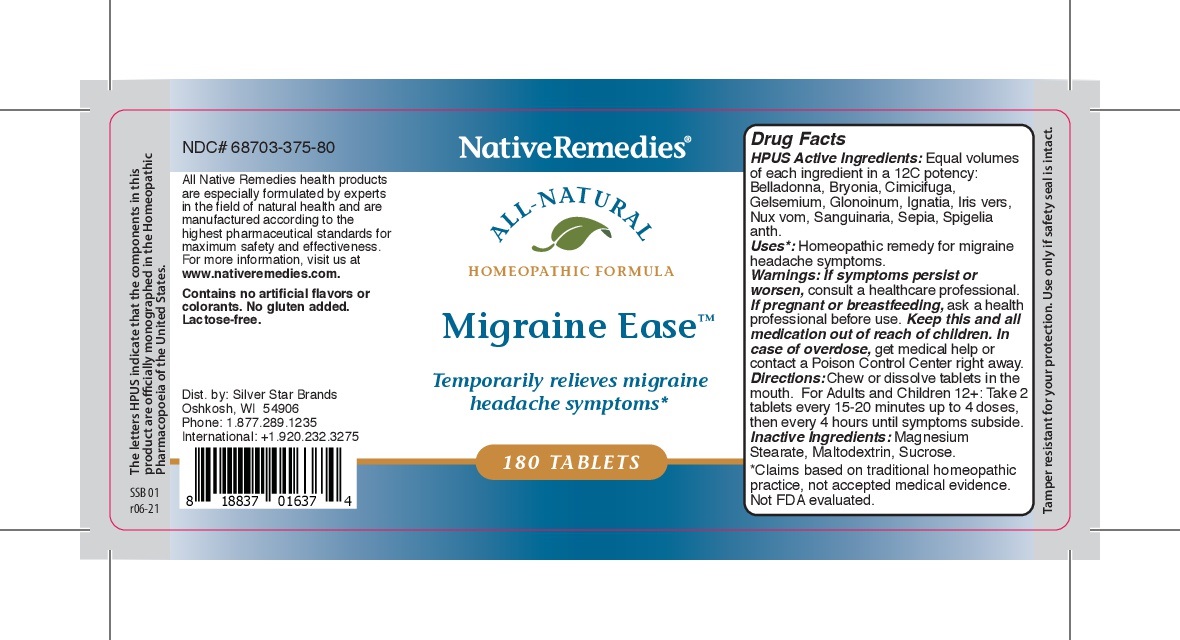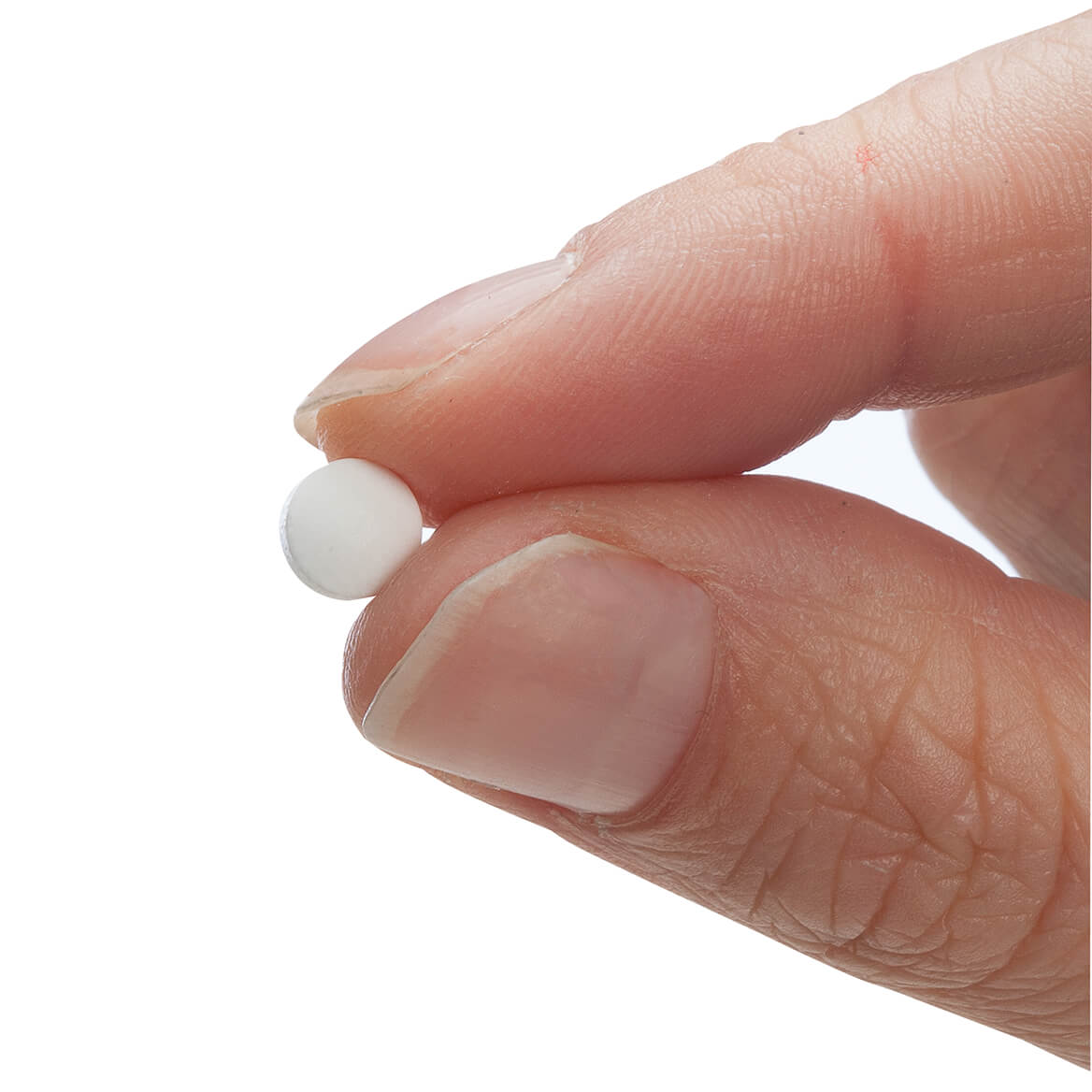 DRUG LABEL: Migraine Ease
NDC: 68703-375 | Form: TABLET
Manufacturer: Silver Star Brands
Category: homeopathic | Type: HUMAN OTC DRUG LABEL
Date: 20250101

ACTIVE INGREDIENTS: ATROPA BELLADONNA 12 [hp_C]/180 1; SPIGELIA ANTHELMIA 12 [hp_C]/180 1; SANGUINARIA CANADENSIS ROOT 12 [hp_C]/180 1; IRIS VERSICOLOR ROOT 12 [hp_C]/180 1; STRYCHNOS NUX-VOMICA SEED 12 [hp_C]/180 1; BRYONIA ALBA ROOT 12 [hp_C]/180 1; NITROGLYCERIN 12 [hp_C]/180 1; SEPIA OFFICINALIS JUICE 12 [hp_C]/180 1; ACTAEA CIMICIFUGA ROOT 12 [hp_C]/180 1; GELSEMIUM SEMPERVIRENS ROOT 12 [hp_C]/180 1; STRYCHNOS IGNATII SEED 12 [hp_C]/180 1
INACTIVE INGREDIENTS: MAGNESIUM STEARATE; MALTODEXTRIN; SUCROSE

NativeRemedies® Migraine Ease Tablets

HPUS Active Ingredients: Equal volumes of each ingredient in a 12C potency: Belladonna, Bryonia, Cimicifuga, Gelsemium, Glonoinum, Ignatia, Iris vers, Nux vom, Sanguinaria, Sepia, Spigelia anth.

Uses*

Uses*: Homeopathic remedy for migraine headache symptoms.

*Claims based on traditional homeopathic practice, not accpeted medical evidence. Not FDA evaluated.

Warnings

Warnings: If symptoms persist or worsen, consult a healthcare professional. If pregnant or breastfeeding, ask a health professional before use. keep this and all medication out of reach of children. In case of overdose, get medical help or contact a Poison Control center right away.

Directions

Directions: Chew or dissolve tablets in the mouth. For Adults and Children 12+: Take 2 tablets every 15-20 minutes up to 4 doses, then every 4 hours until symptoms subside.

OTHER SAFETY INFORMATION

Contains no artificial flavors or colorants. No gluten added. Lactose-free.

Tamper resistant for your protection. use only if safety seal is intact.

Inactive Ingredients

Inactive Ingredients: Magnesium Stearate, Maltodextrin, Sucrose.

KEEP OUT OF REACH OF CHILDREN

Keep this and all medication out of reach of children.

PREGNANCY OR BREAST FEEDING

If pregnant or breastfeeding, ask a health professional before use.

PURPOSE

Temporarily relieves migraine headache symptoms*

*Claims based on traditional homeopathic practice, not accepted medical evidence. Not FDA evaluated.